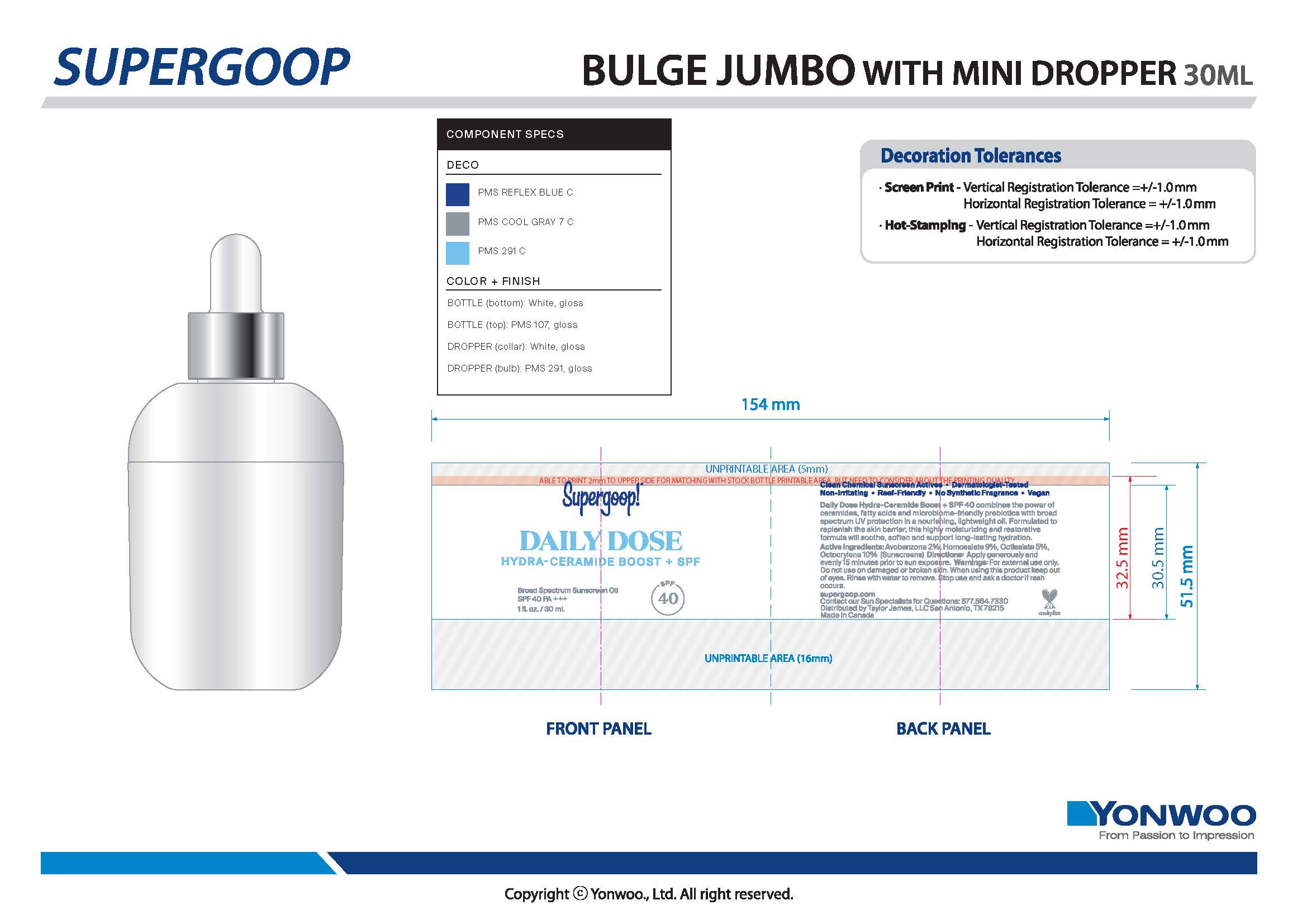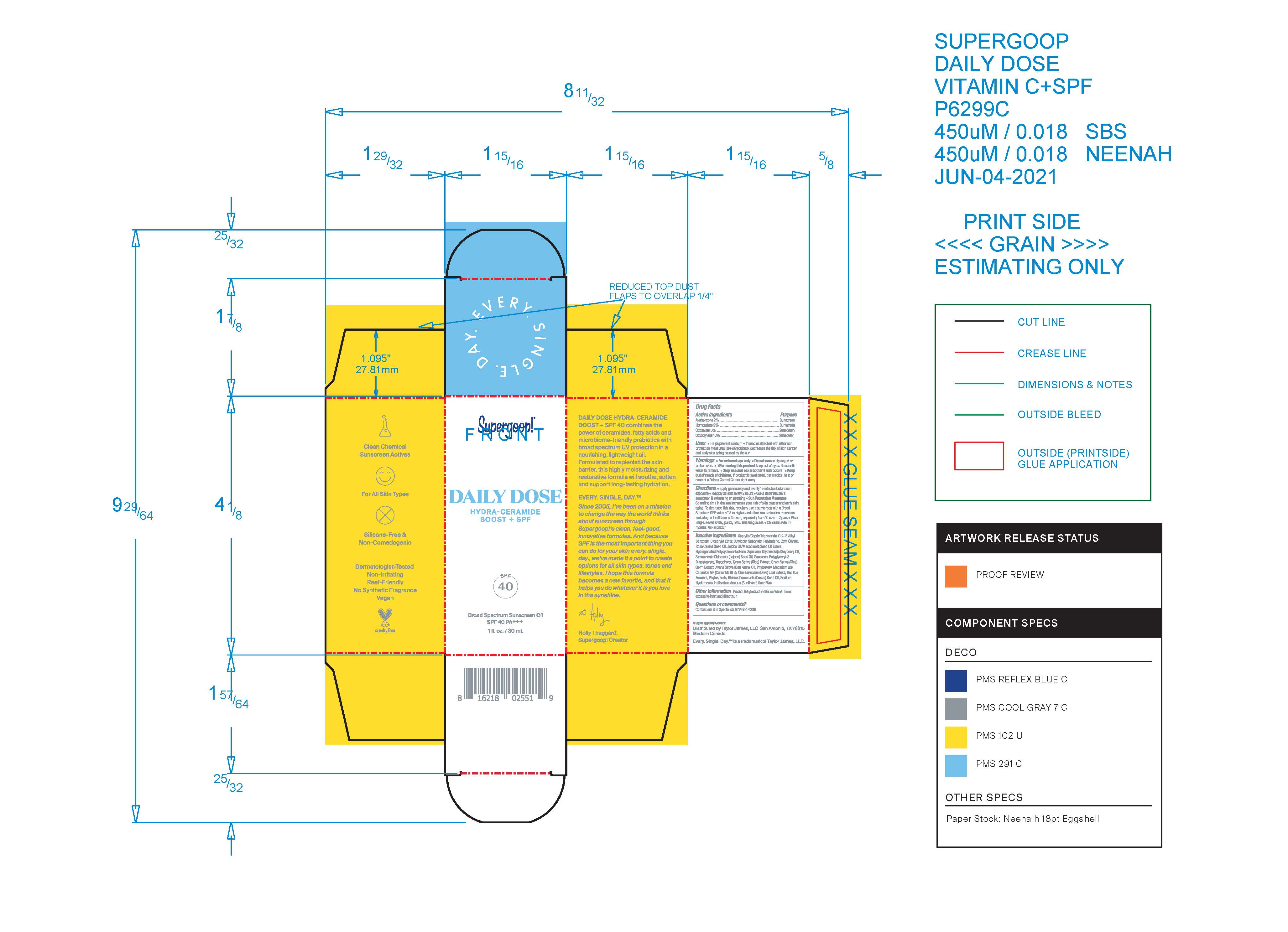 DRUG LABEL: Daily Dose Hydra-Ceramide Boost  Broad Spectrum Sunscreen SPF 40
NDC: 75936-306 | Form: OIL
Manufacturer: Supergoop, LLC
Category: otc | Type: HUMAN OTC DRUG LABEL
Date: 20241216

ACTIVE INGREDIENTS: AVOBENZONE 2 g/100 mL; HOMOSALATE 9 g/100 mL; OCTOCRYLENE 10 g/100 mL; OCTISALATE 5 g/100 mL
INACTIVE INGREDIENTS: POLYGLYCERYL-3 DIISOSTEARATE; TOCOPHEROL; JOJOBA OIL; BUTYLOCTYL SALICYLATE; ETHYL OLIVATE; ROSA CANINA SEED OIL; SQUALANE; OLEA EUROPAEA LEAF; SOYBEAN OIL; CERAMIDE NP; HELIANTHUS ANNUUS SEED WAX; POLYBUTENE (1400 MW); SQUALENE; MEDIUM-CHAIN TRIGLYCERIDES; ALKYL (C12-15) BENZOATE; DICAPRYLYL ETHER; CASTOR OIL; HYALURONATE SODIUM; OAT KERNEL OIL; PHYTOSTERYL MACADAMIATE; RICE GERM

Daily Dose Hydra-Ceramide Boost Broad Spectrum Sunscreen SPF 40

Active Ingredients Purpose

Avobenzone 2% Sunscreen

Homosalate 9% Sunscreen

Octisalate 5% Sunscreen

Octocrylene 10% Sunscreen

Uses

- Helps prevent sunburn
- If used as directed with other sun protection measures (see Directions), decreases the risk of skin cancer and early skin aging caused by the sun

- Keep out of reach of children. If product is swallowed, get medical help or contact a Poison Control Center right away.

Stop use and ask a doctor if rash occurs.

Warnings

- For external use only
- Do not use on damaged or broken skin
- When using this product keep out of eyes. Rinse with water to remove

Directions

- apply generously and evenly 15 minutes before sun exposure
- reapply at least every 2 hours
- Use a water resistant Sunscreen if swimming or sweating
- Sun Protection Measures Spending time in the sun increases your risk of skin cancer and early skin aging. To decrease this risk, regularly use a sunscreen with a Broad Spectrum SPF value of 15 or higher and other sun protection measures including
- Limit time in the sun, especially from 10 a.m. - 2 p.m.
- Wear long-sleeved shirts, pants, hats, and sun glasses
- Children under 6 months: Ask a doctor

INACTIVE INGREDIENT

Inactive Ingredients Caprylic/Capric Triglyceride, C12-15 Alkyl Benzoate, Dicaprylyl Ether, Butyloctyl Salicylate, Polybutene, Ethyl Olivate, Rosa Canina Seed Oil, Jojoba Oil/ Macadamia Seed Oil Esters, Hydrogenated Polycyclopentadiene, Squalane, Glycine Soja (Soybean) Oil, Simmondsia Chinensis (Jojoba) Seed Oil, Squalene, Polyglyceryl-3 Diisostearate, Tocopherol, Oryza Sativa (Rice) Extract, Oryza Sativa (Rice) Germ Extract, Avena Sativa (Oat) Kernel Oil, Phytosteryl Macadamiate, Ceradmide NP (Ceramide III B), Olea Europaea (Olive) Leaf Extract, Bacillus Ferment, Phytosterols, Ricinus communis (Castor) Seed Oil, Sodium Hyaluronate, Helianthus Annuus (Sunflower) Seed Wax

PACKAGE LABEL

Supergoop

DAILY DOSE

HYDRA-CERAMIDE BOOST + SPF

SPF 40

Broad Spectrum Sunscreen Oil

SPF 40 PA+++

1 fl. oz. / 30 ml.